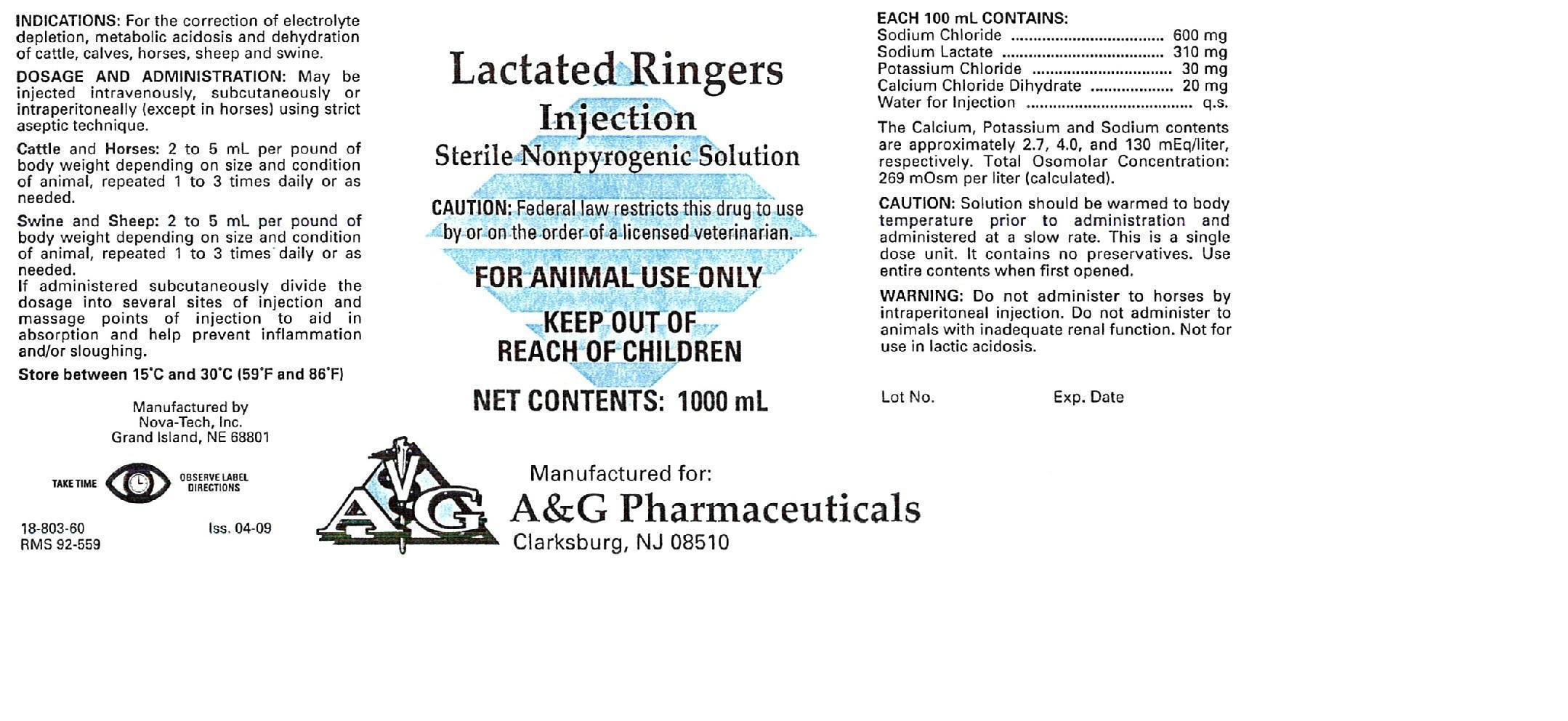 DRUG LABEL: Lactated Ringers
                        
NDC: 57699-803 | Form: INJECTION, SOLUTION
Manufacturer: A & G Pharmaceuticals, Inc.
Category: animal | Type: PRESCRIPTION ANIMAL DRUG LABEL
Date: 20240424

ACTIVE INGREDIENTS: Sodium Chloride 600 mg/1000 mL; Sodium Lactate 310 mg/1000 mL; Potassium Chloride 30 mg/1000 mL; Calcium Chloride 20 mg/1000 mL

Lactated Ringers Injection

PRECAUTIONS

CAUTION: Federal law restricts this drug to use by or on the order of a licensed veterinarian.
FOR ANIMAL USE ONLY
KEEP OUT OF REACH OF CHILDREN
NET CONTENTS: 1000 mL

INDICATIONS:

For the correction of electrolyte depletion, metabolic acidosis and dehydration of cattle, calves, horses, sheep and swine.

DOSAGE AND ADMINISTRATION:

May be injected intravenously, subcutaneously or intraperitoneally (except in horses) using strict aseptic technique.

Cattle and Horses: 2 to 5 mL per pound of body weight depending on size and condition of animal, repeated 1 to 3 times daily or as needed.

Swine and Sheep: 2 to 5 mL per pound of body weight depending on size and condition of animal, repeated 1 to 3 times daily or as needed.

If administered subcutaneously divide the dosage into several sites of injection and massage points of injection to aid in absorption and help prevent inflammation and/or sloughing.

STORAGE AND HANDLING

Store between 15°C - 30°C (59°F - 86°F)

DOSAGE FORMS AND STRENGTHS

EACH 100 mL CONTAINS:

Sodium Chloride....................600 mg

Sodium Lactate.....................310 mg

Potassium Chloride.................30 mg

Calcium Chloride Dihydrate......20 mg

Water for Injection.......................q.s.

The Calcium, Potassium and Sodium contents are approximately 2.7, 4.0 and 130 mEq/liter, respectively. Total Osmolar Concentration: 269 mOsm per liter (calculated).

CAUTION:

Solution should be warmed to body temperature prior to administration and administered at a slow rate. This is a single dose unit. It contains no preservatives. Use entire contents when first opened.

WARNING:

Do not administer to horses by intraperitoneal injection. Do not administer to animals with inadequate renal function. Not for use in lactic acidosis.

INFORMATION FOR OWNERS/CAREGIVERS

Manufactured by

Nova-Tech, Inc.

Grand Island, NE 68801

TAKE TIME OBSERVE LABEL DIRECTIONS

18-803-60

RMS 92-559

Iss. 04-09

Manufactured for:

A&G Pharmaceuticals

Clarksburg, NJ 08510

Lot No.

Exp. Date